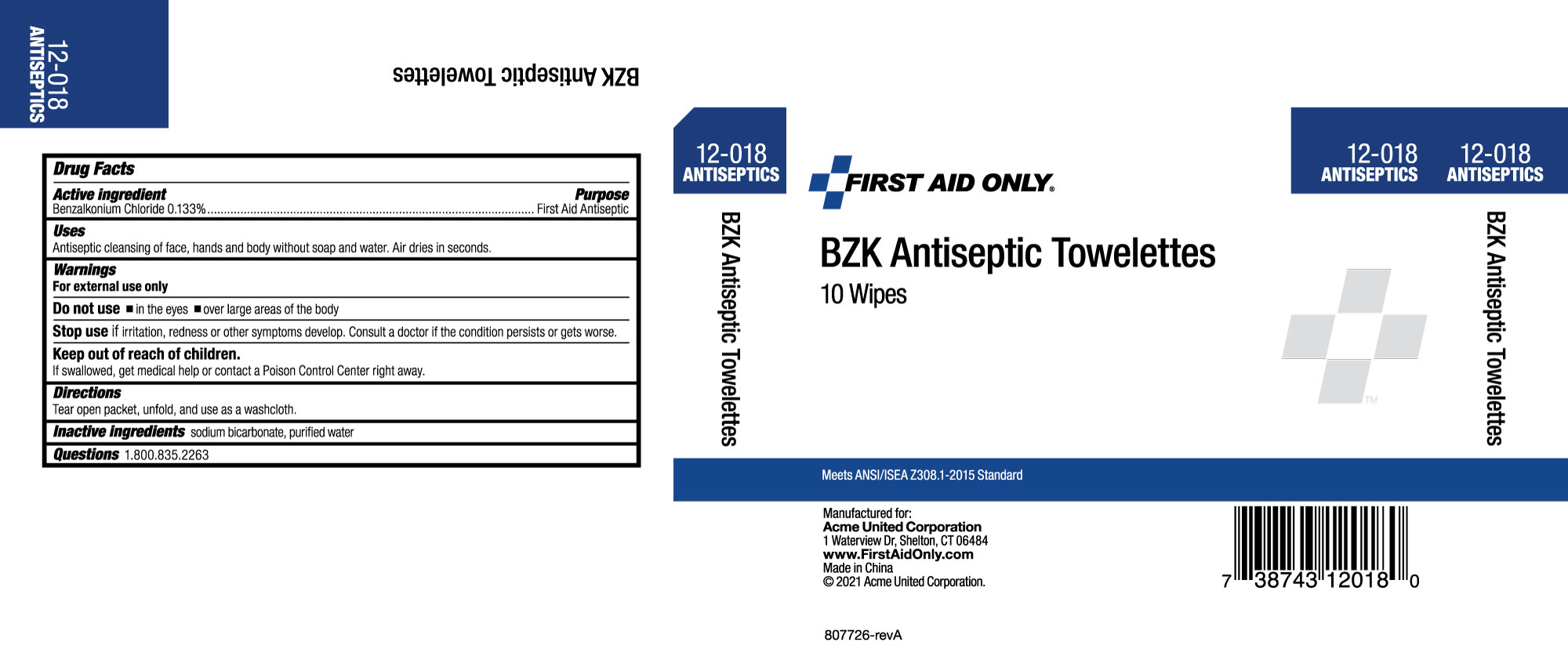 DRUG LABEL: First Aid Only BZK Antiseptic Towelettes
NDC: 0924-7115 | Form: LIQUID
Manufacturer: Acme United Corporation
Category: otc | Type: HUMAN OTC DRUG LABEL
Date: 20241015

ACTIVE INGREDIENTS: BENZALKONIUM CHLORIDE 1.3 mg/1 mL
INACTIVE INGREDIENTS: WATER; SODIUM BICARBONATE

First Aid Only BZK Antiseptic Towelette

Active ingredient

Benzalkonium Chloride 0.133%

Purpose

First Aid Antiseptic

Uses

Antiseptic cleansing of face, hands, and body without soap and water. Air dries in seconds.

Warnings

Do not use

- in the eyes
- over large areas of the body.

Stop use

- if irritation, redness, or other symptoms develop. Consult a doctor if the condition persists or gets worse.

Keep out of reach of children.

If swallowed, get medical help or contact a Poison Control center right away.

Directions

Tear open packet, unfold, and use as a washcloth.

Inactive ingredients

Purified Water, sodium bicarbonate

Questions

1-800-835-2263

carton label